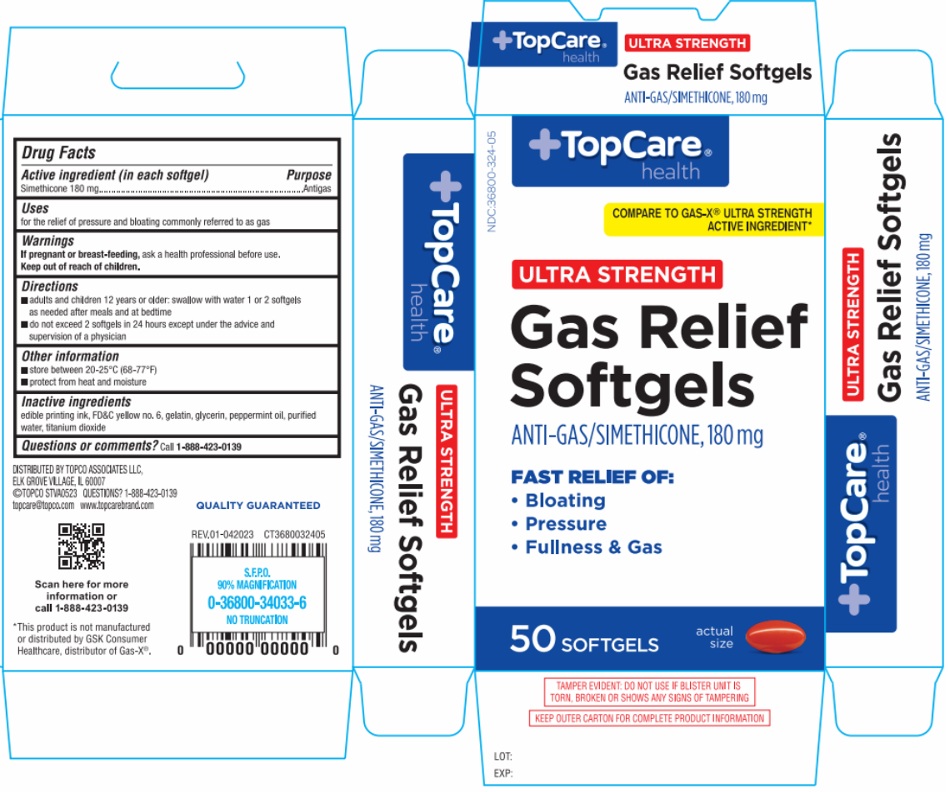 DRUG LABEL: Gas Relief Ultra Strength
NDC: 36800-324 | Form: CAPSULE, LIQUID FILLED
Manufacturer: TOPCO ASSOCIATES LLC
Category: otc | Type: HUMAN OTC DRUG LABEL
Date: 20241214

ACTIVE INGREDIENTS: DIMETHICONE, UNSPECIFIED 180 mg/1 1
INACTIVE INGREDIENTS: FD&C YELLOW NO. 6; GELATIN, UNSPECIFIED; GLYCERIN; PEPPERMINT OIL; WATER; TITANIUM DIOXIDE

Gas Relief Ultra Strength

Active ingredient (in each softgel)

Simethicone 180 mg

Purpose

Antigas

Uses

for the relief of pressure and bloating commonly referred to as gas

Warnings

If pregnant or breast-feeding, ask a health professional before use.

Keep out of reach of children.

Directions

- adults and children 12 years or older: swallow with water 1 or 2 softgels as needed after meals and at bedtime
- do not exceed 2 softgels in 24 hours except under the advice and supervision of a physician

Other information

- store between 20-25°C (68-77°F)
- protect from heat and moisture

Inactive ingredients

edible printing ink, FD&C yellow no. 6, gelatin, glycerin, peppermint oil, purified water, titanium dioxide

Questions or comments?

Call 1-888-423-0139

TopCare® health

COMPARE TO GAS-X® ULTRA STRENGTH ACTIVE INGREDIENT*

FAST RELIEF OF:
• Bloating
• Pressure
• Fullness & Gas

DISTRIBUTED BY TOPCO ASSOCIATES LLC,
ELK GROVE VILLAGE, I. 60007
©TOPCO STVA0523
topcare@topco.com www.topcarebrand.com

*This product is not manufactured or distributed by GSK Consumer Healthcare, distributor of Gas-X®.

QUALITY GUARANTEED

TAMPER EVIDENT: DO NOT USE IF BLISTER UNIT IS TORN, BROKEN OR SHOWS ANY SIGNS OF TAMPERING

KEEP OUTER CARTON FOR COMPLETE PRODUCT INFORMATION